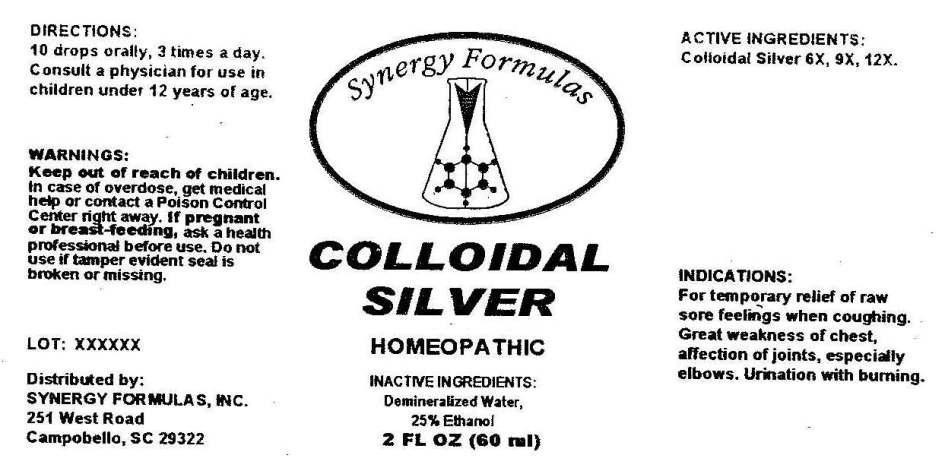 DRUG LABEL: Colloidal Silver
NDC: 43772-0010 | Form: LIQUID
Manufacturer: Synergy Formulas, Inc.
Category: homeopathic | Type: HUMAN OTC DRUG LABEL
Date: 20130402

ACTIVE INGREDIENTS: SILVER 6 [hp_X]/1 mL
INACTIVE INGREDIENTS: WATER; ALCOHOL

Drug Facts

ACTIVE INGREDIENTS

Colloidal Silver 6X, 9X, 12X

INDICATIONS

For temporary relief of raw sore feelings when coughing. Great weakness of chest, affection of joints, especially elbows. Urination with burning.

WARNINGS

Keep out of reach of children. In case of overdose, get medical help or contact a Poison Control Center right away. If pregnant or breast-feeding, ask a health professional before use. Do not use if tamper evident seal is broken or missing.

DIRECTIONS

10 drops orally, 3 times a day. Consult a physician for use in children under 12 years of age.

INACTIVE INGREDIENTS

Demineralized Water, 25% Ethanol

KEEP OUT OF REACH OF CHILDREN

In case of overdose, get medical help or contact a Poison Control Center right away.

INDICATIONS AND USAGE

For temporary relief of raw sore feelings when coughing. Great weakness of chest, affection of joints, especially elbows. Urination with burning.

QUESTIONS

Distributed by:

SYNERGY FORMULAS, INC.

251 West Road

Campobello, SC 29322

PACKAGE LABEL

Synergy Formulas

COLLOIDAL SILVER

HOMEOPATHIC

2 FL OZ (60 ml)